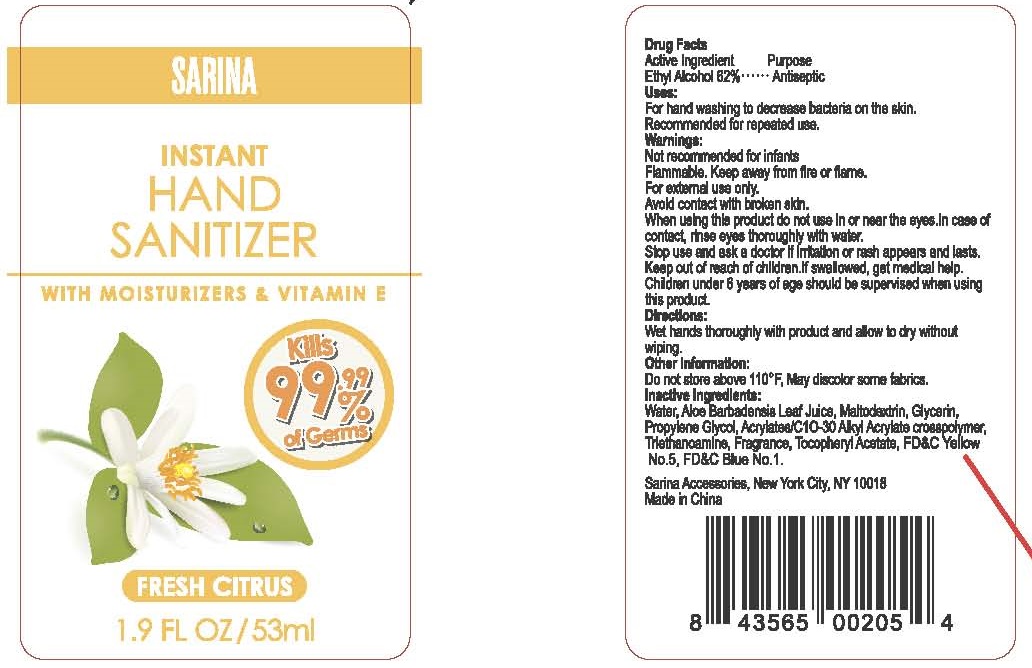 DRUG LABEL: Hand Sanitizer
NDC: 90106-001 | Form: GEL
Manufacturer: Sarina Accessories, LLC
Category: otc | Type: HUMAN OTC DRUG LABEL
Date: 20200807

ACTIVE INGREDIENTS: ALCOHOL 62 mL/100 mL
INACTIVE INGREDIENTS: MALTODEXTRIN; ALOE VERA LEAF; WATER; GLYCERIN; PROPYLENE GLYCOL; CARBOMER COPOLYMER TYPE A (ALLYL PENTAERYTHRITOL CROSSLINKED); FD&C YELLOW NO. 5; TROLAMINE; .ALPHA.-TOCOPHEROL ACETATE; FD&C BLUE NO. 1

Active Ingredient

Ethyl Alcohol 62%

Purpose

Antiseptic

Uses:

For hand washing to decrease bacteria on the skin.

Recommended for repeated use.

Warnings:

Not recommended for infants.

Flammable. Keep away from fire or flame.

For external use only.

Avoid contact with broken skin.

When using this product do not use in or near the eyes. In case of contact, rinse eyes thoroughly with water.

Stop use and ask a doctor if irritation or rash appears and lasts.

Keep out of reach of children. If swallowed, get medical help.

Children under 6 years of age should be supervised when using this product.

Directions

Wet hands thoroughly with product and allow to dry without wiping.

.

Other Information

Do not store above 110 °F, May discolor some fabrics.

Inactive Ingredients

Water, Aloe Barbadensis Leaf Juice, Maltodextrin, Glycerin, Propylene Glycol, Acrylates/C 10-30 Alkyl Acrylate crosspolymer, Triethanoamine, Fragrance, Tocopheryl Acetate, FD&C Yellow No. 5. FD&C Blue No.1